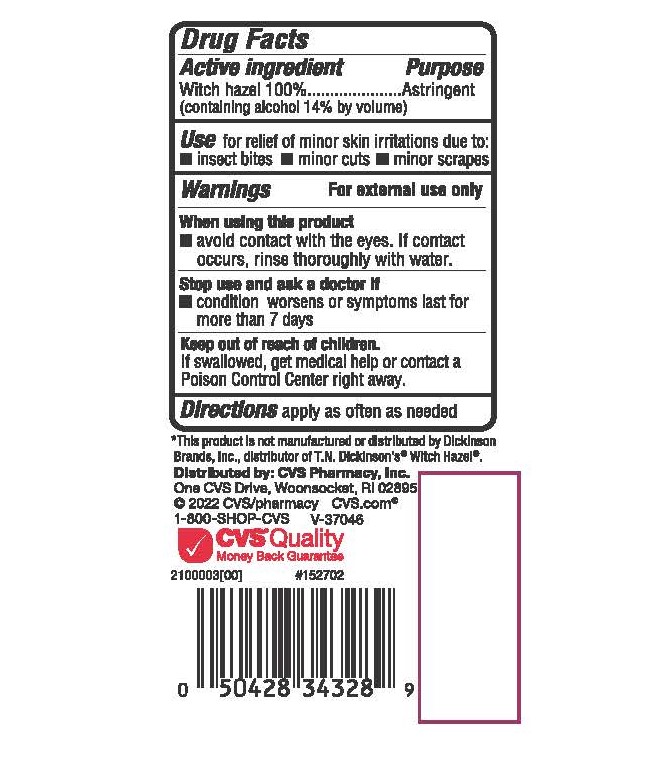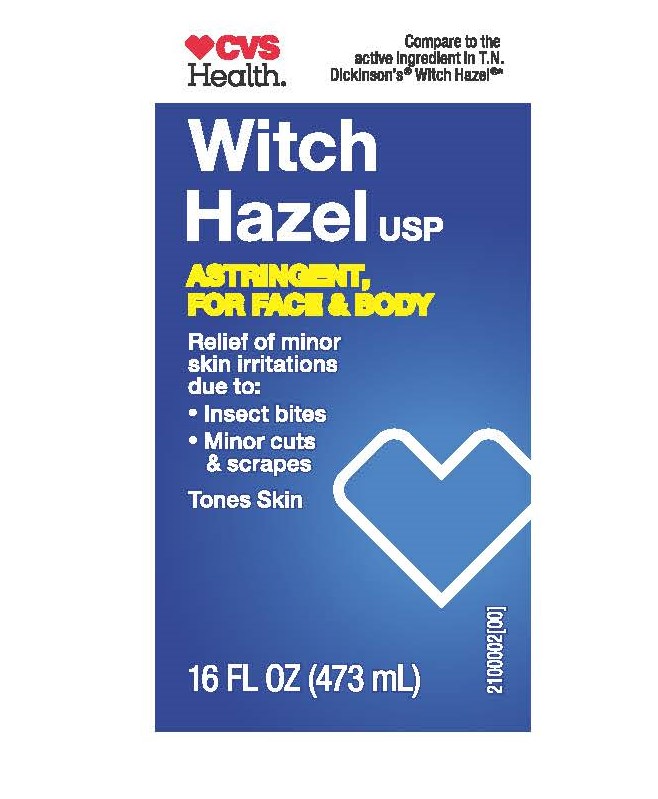 DRUG LABEL: Witch Hazel
NDC: 69842-330 | Form: LIQUID
Manufacturer: CVS HEALTH
Category: otc | Type: HUMAN OTC DRUG LABEL
Date: 20251229

ACTIVE INGREDIENTS: WITCH HAZEL 84 g/100 mL
INACTIVE INGREDIENTS: ALCOHOL

CVS Witch Hazel

ACTIVE INGREDIENT

Witch Hazel 100% (Containing alcohol 14% by Volume)

PURPOSE

Astringent

INDICATIONS AND USAGE

Use for relief of minor skin irritations due to

- Insect bites
- minor cuts
- minor scrapes

WARNINGS

For External use only

WHEN USING

Avoid contact with eyes. If contact occurs, rinse thoroughly with water

Stop use and ask a doctor if

- condition worsens or symptoms last for more than 7 days

KEEP OUT OF REACH OF CHILDREN

If swallowed, get medical help or contact a Poison Control right away

DOSAGE AND ADMINISTRATION

Apply as often as needed

INACTIVE INGREDIENT

Alcohol